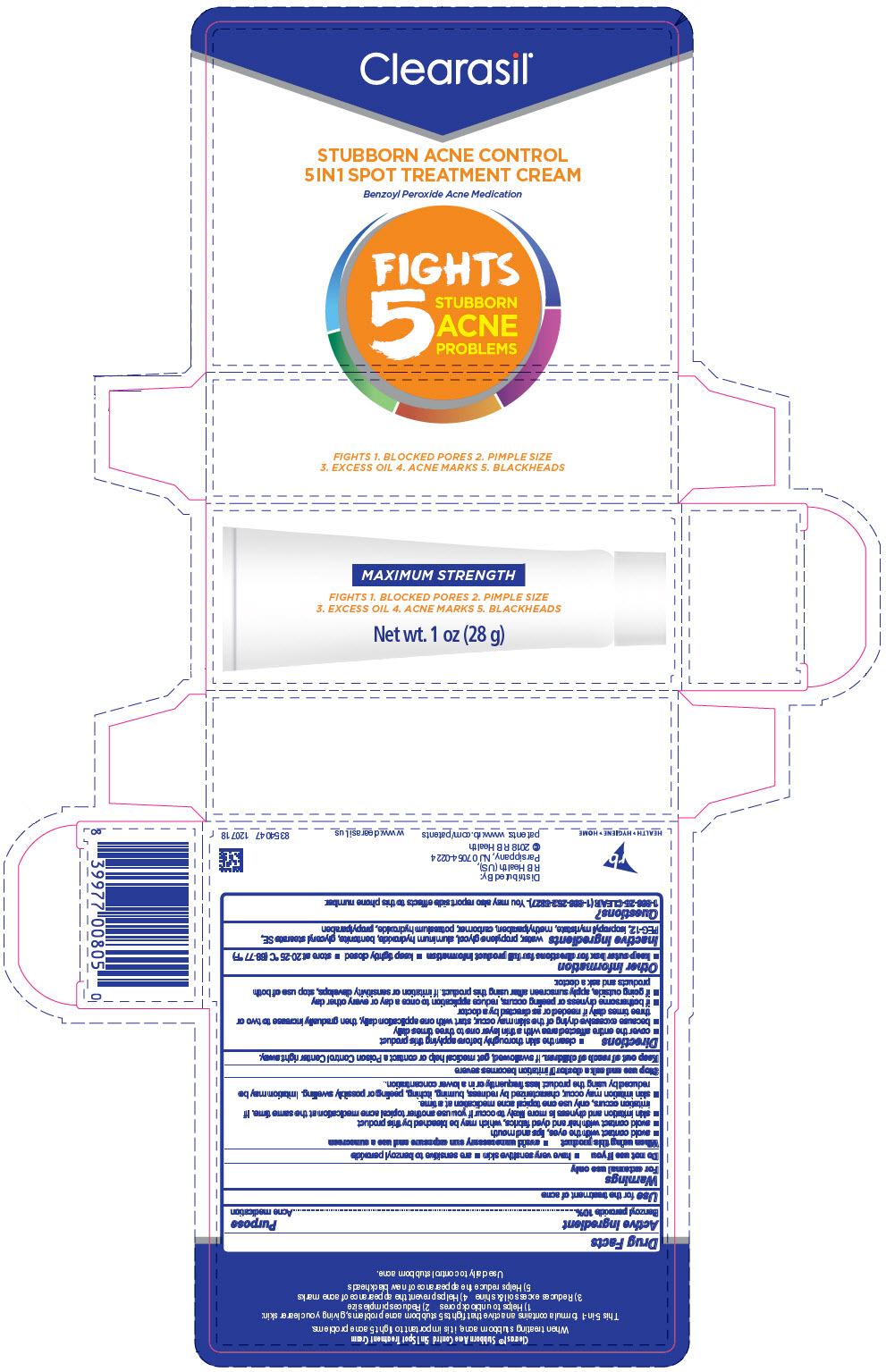 DRUG LABEL: Clearasil Stubborn Acne Control 5in1 Spot Treatment
NDC: 63824-438 | Form: CREAM
Manufacturer: RB Health (US) LLC
Category: otc | Type: HUMAN OTC DRUG LABEL
Date: 20241218

ACTIVE INGREDIENTS: BENZOYL PEROXIDE 10 g/100 g
INACTIVE INGREDIENTS: WATER; PROPYLENE GLYCOL; ALUMINUM HYDROXIDE; BENTONITE; GLYCERYL STEARATE SE; POLYETHYLENE GLYCOL 600; ISOPROPYL MYRISTATE; METHYLPARABEN; CARBOMER HOMOPOLYMER, UNSPECIFIED TYPE; POTASSIUM HYDROXIDE; PROPYLPARABEN

Clearasil®Stubborn Acne Control 5in1 Spot Treatment Cream

Drug Facts

Active ingredient

Benzoyl peroxide 10%

Purpose

Acne medication

Use

for the treatment of acne

Warnings

For external use only

Do not useif you

- have very sensitive skin
- are sensitive to benzoyl peroxide

When using this product

- avoid unnecessary sun exposure and use a sunscreen
- avoid contact with the eyes, lips and mouth
- avoid contact with hair and dyed fabrics, which may be bleached by this product
- skin irritation and dryness is more likely to occur if you use another topical acne medication at the same time. If irritation occurs, only use one topical acne medication at a time.
- skin irritation may occur, characterized by redness, burning, itching, peeling or possibly swelling. Irritation may be reduced by using the product less frequently or in a lower concentration.

Stop use and ask a doctor ifirritation becomes severe

Keep out of reach of children.If swallowed, get medical help or contact a Poison Control Center right away.

Directions

- clean the skin thoroughly before applying this product
- cover the entire affected area with a thin layer one to three times daily
- because excessive drying of the skin may occur, start with one application daily, then gradually increase to two or three times daily if needed or as directed by a doctor
- if bothersome dryness or peeling occurs, reduce application to once a day or every other day
- if going outside, apply sunscreen after using this product. If irritation or sensitivity develops, stop use of both products and ask a doctor.

Other information

- keep outer box for full product information
- keep tightly closed
- store at 20-25 °C (68-77 °F)

Inactive ingredients

Water, Propylene Glycol, Aluminum Hydroxide, Bentonite, Glyceryl Stearate SE, PEG-12, Isopropyl Myristate, Methylparaben, Carbomer, Potassium Hydroxide, Propylparaben

Questions?

1-866-25-CLEAR (1-866-252-5327).You may also report side effects to this phone number.

Distributed By:
RB Health (US),
Parsippany, NJ 07054-0224

PRINCIPAL DISPLAY PANEL - 28 g Tube Carton

Clearasil®

STUBBORN ACNE CONTROL
5IN1 SPOT TREATMENT CREAM

Benzoyl Peroxide Acne Medication

FIGHTS
5
STUBBORN
ACNE
PROBLEMS

MAXIMUM STRENGTH

FIGHTS 1. BLOCKED PORES 2. PIMPLE SIZE
3. EXCESS OIL 4. ACNE MARKS 5. BLACKHEADS

Net wt. 1 oz (28 g)